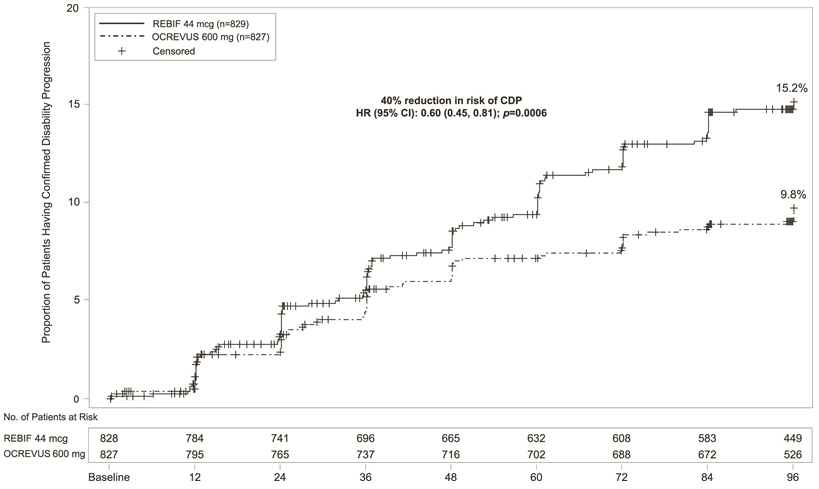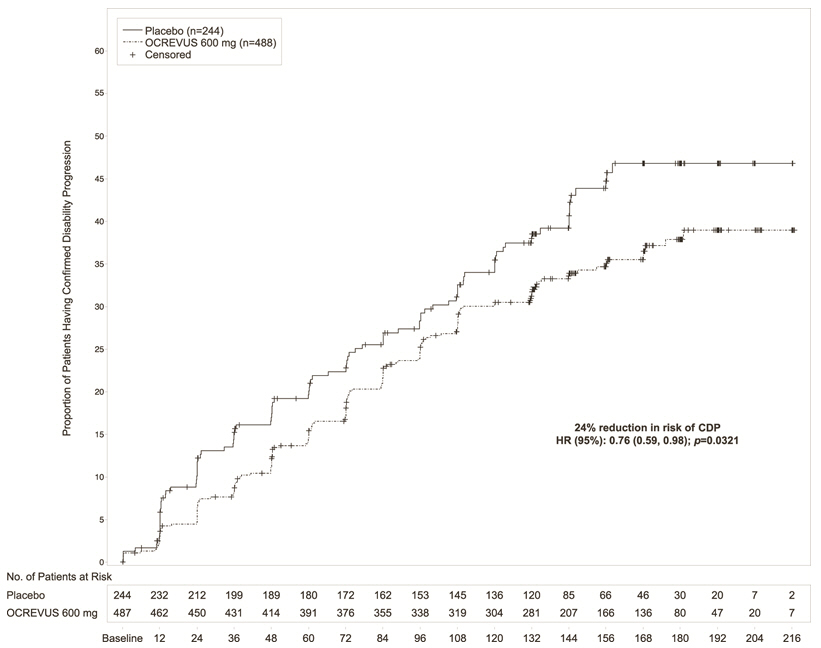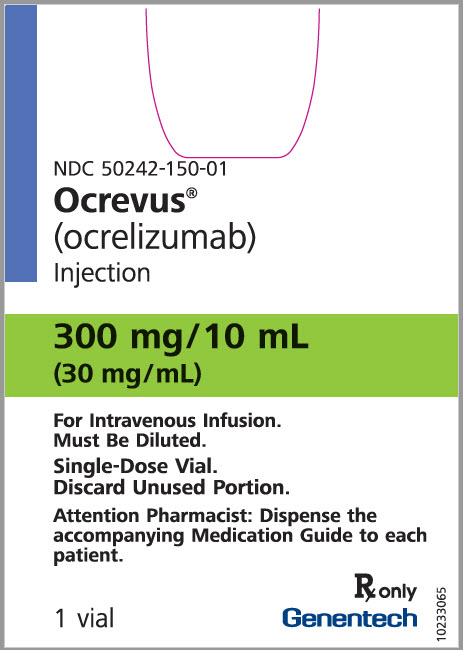 DRUG LABEL: OCREVUS
NDC: 50242-150 | Form: INJECTION
Manufacturer: Genentech, Inc.
Category: prescription | Type: HUMAN PRESCRIPTION DRUG LABEL
Date: 20251209

ACTIVE INGREDIENTS: OCRELIZUMAB 300 mg/10 mL
INACTIVE INGREDIENTS: SODIUM ACETATE 21.4 mg/10 mL; ACETIC ACID 2.5 mg/10 mL; TREHALOSE DIHYDRATE 400 mg/10 mL; POLYSORBATE 20 2 mg/10 mL; WATER

HIGHLIGHTS OF PRESCRIBING INFORMATION

These highlights do not include all the information needed to use OCREVUS safely and effectively. See full prescribing information for OCREVUS.
OCREVUS® (ocrelizumab) injection, for intravenous use
Initial U.S. Approval: 2017

RECENT MAJOR CHANGES

Dosage and Administration (2.1) | 8/2025
Warnings and Precautions (5.7) | 8/2025

1 INDICATIONS AND USAGE

OCREVUS is a CD20-directed cytolytic antibody indicated for the treatment of:

- Relapsing forms of multiple sclerosis (MS), to include clinically isolated syndrome, relapsing-remitting disease, and active secondary progressive disease, in adults (1)
- Primary progressive MS, in adults (1)

2 DOSAGE AND ADMINISTRATION

- Before initiating OCREVUS, screen for Hepatitis B virus and obtain serum quantitative immunoglobulins, aminotransferases, alkaline phosphatase, and bilirubin (2.1)
- Pre-medicate with methylprednisolone (or an equivalent corticosteroid) and an antihistamine (e.g., diphenhydramine) prior to each infusion (2.2)
- Administer OCREVUS by intravenous infusion
  - Start dose: 300 mg intravenous infusion, followed two weeks later by a second 300 mg intravenous infusion (2.3)
  - Subsequent doses: 600 mg intravenous infusion every 6 months (2.3)
- Must be diluted prior to administration (2.3, 2.6)
- Monitor patients closely during and for at least one hour after infusion (2.3, 2.5)

3 DOSAGE FORMS AND STRENGTHS

- Injection: 300 mg/10 mL (30 mg/mL) in a single-dose vial (3)

4 CONTRAINDICATIONS

- Active hepatitis B virus infection (4)
- History of life-threatening infusion reaction to OCREVUS (4)

5 WARNINGS AND PRECAUTIONS

- Infusion Reactions: Management recommendations for infusion reactions depend on the type and severity of the reaction. Permanently discontinue OCREVUS if a life-threatening or disabling infusion reaction occurs (2.3, 5.1)
- Infections: Serious, including life-threatening and fatal infections, have occurred. Delay OCREVUS administration in patients with an active infection until the infection is resolved. Vaccination with live-attenuated or live vaccines is not recommended during treatment with OCREVUS and after discontinuation, until B-cell repletion (5.2)
- Progressive Multifocal Leukoencephalopathy (PML): Withhold OCREVUS at the first sign or symptom suggestive of PML (5.3)
- Reduction in Immunoglobulins: Monitor the level of immunoglobulins at the beginning of treatment. Monitor during and after discontinuation of treatment with OCREVUS, until B-cell repletion, and especially when recurrent serious infections are suspected. Consider discontinuing OCREVUS in patients with serious opportunistic or recurrent serious infections, and if prolonged hypogammaglobulinemia requires treatment with intravenous immunoglobulins (2.1, 5.4)
- Malignancies: An increased risk of malignancy, including breast cancer, may exist with OCREVUS (5.5)
- Immune-Mediated Colitis: Immune-mediated colitis has been reported in the postmarketing setting. Monitor patients for new or persistent diarrhea or other gastrointestinal symptoms, and evaluate promptly if colitis is suspected (5.6)
- Liver Injury: Clinically significant liver injury has occurred. Obtain serum aminotransferases, alkaline phosphatase, and bilirubin levels before initiating OCREVUS, and during treatment as clinically indicated. Discontinue OCREVUS in patients with evidence of liver injury in the absence of an alternative etiology (5.7).

6 ADVERSE REACTIONS

The most common adverse reactions were:

- RMS (incidence ≥10% and > REBIF®): upper respiratory tract infections and infusion reactions (6.1)
- PPMS (incidence ≥10% and > placebo): upper respiratory tract infections, infusion reactions, skin infections, and lower respiratory tract infections (6.1)

To report SUSPECTED ADVERSE REACTIONS, contact Genentech at 1-888-835-2555 or FDA at 1-800-FDA-1088 or www.fda.gov/medwatch.

8 USE IN SPECIFIC POPULATIONS

- Pregnancy: Based on animal data, may cause fetal harm (8.1)

FULL PRESCRIBING INFORMATION

1 INDICATIONS AND USAGE

OCREVUS is indicated for the treatment of:

- Relapsing forms of multiple sclerosis (MS), to include clinically isolated syndrome, relapsing-remitting disease, and active secondary progressive disease, in adults
- Primary progressive MS, in adults

2 DOSAGE AND ADMINISTRATION

2.1 Assessments Prior to First Dose of OCREVUS

Hepatitis B Virus Screening

Prior to initiating OCREVUS, perform Hepatitis B virus (HBV) screening. OCREVUS is contraindicated in patients with active HBV confirmed by positive results for HBsAg and anti-HBV tests. For patients who are negative for surface antigen [HBsAg] and positive for HB core antibody [HBcAb+] or are carriers of HBV [HBsAg+], consult liver disease experts before starting and during treatment [see Warnings and Precautions (5.2)].

Serum Immunoglobulins
Prior to initiating OCREVUS, perform testing for quantitative serum immunoglobulins [see Warnings and Precautions (5.4)]. For patients with low serum immunoglobulins, consult immunology experts before initiating treatment with OCREVUS.

Vaccinations

Because vaccination with live-attenuated or live vaccines is not recommended during treatment and after discontinuation until B-cell repletion, administer all immunizations according to immunization guidelines at least 4 weeks prior to initiation of OCREVUS for live or live-attenuated vaccines and, whenever possible, at least 2 weeks prior to initiation of OCREVUS for non-live vaccines [see Warnings and Precautions (5.2) and Clinical Pharmacology (12.2)].

Liver Function Tests

Prior to initiating OCREVUS, obtain serum aminotransferases (alanine aminotransferase [ALT] and aspartate aminotransferase [AST]), alkaline phosphatase, and bilirubin levels [see Warnings and Precautions (5.7)].

2.2 Preparation Before Every Infusion

Infection Assessment

Prior to every infusion of OCREVUS, determine whether there is an active infection. In case of active infection, delay infusion of OCREVUS until the infection resolves [see Warnings and Precautions (5.2)].

Recommended Premedication

Pre-medicate with 100 mg of methylprednisolone (or an equivalent corticosteroid) administered intravenously approximately 30 minutes prior to each OCREVUS infusion to reduce the frequency and severity of infusion reactions [see Warnings and Precautions (5.1)]. Pre-medicate with an antihistamine (e.g., diphenhydramine) approximately 30-60 minutes prior to each OCREVUS infusion to further reduce the frequency and severity of infusion reactions.

The addition of an antipyretic (e.g., acetaminophen) may also be considered.

2.3 Recommended Dosage and Dose Administration

Administer OCREVUS under the close supervision of an experienced healthcare professional with access to appropriate medical support to manage severe reactions such as serious infusion reactions.

- Initial dose: 300 mg intravenous infusion, followed two weeks later by a second 300 mg intravenous infusion.
- Subsequent doses: single 600 mg intravenous infusion every 6 months.
- Observe the patient for at least one hour after the completion of the infusion [see Warnings and Precautions (5.1)].

Table 1 Recommended Dose, Infusion Rate, and Infusion Duration for RMS and PPMS
 |  | Amount and Volume [Solutions of OCREVUS for intravenous infusion are prepared by dilution of the drug product into an infusion bag containing 0.9% Sodium Chloride Injection, to a final drug concentration of approximately 1.2 mg/mL.] | Infusion Rate and Duration [Infusion time may take longer if the infusion is interrupted or slowed [see Dosage and Administration (2.5)].]
Initial Dose (two infusions) | Infusion 1 | 300 mg in 250 mL | - Start at 30 mL per hour - Increase by 30 mL per hour every 30 minutes - Maximum: 180 mL per hour - Duration: 2.5 hours or longer
Initial Dose (two infusions) | Infusion 2 (2 weeks later) | 300 mg in 250 mL | - Start at 30 mL per hour - Increase by 30 mL per hour every 30 minutes - Maximum: 180 mL per hour - Duration: 2.5 hours or longer
Subsequent Doses (one infusion) every 6 months) [Administer the first Subsequent Dose 6 months after Infusion 1 of the Initial Dose.] | Option 1 Infusion of approximately 3.5 hours duration | 600 mg in 500 mL | - Start at 40 mL per hour - Increase by 40 mL per hour every 30 minutes - Maximum: 200 mL per hour - Duration: 3.5 hours or longer
Subsequent Doses (one infusion) every 6 months) [Administer the first Subsequent Dose 6 months after Infusion 1 of the Initial Dose.] | OR
Subsequent Doses (one infusion) every 6 months) [Administer the first Subsequent Dose 6 months after Infusion 1 of the Initial Dose.] | Option 2 (If no prior serious infusion reaction with any previous OCREVUS infusion) [[see Adverse Reactions (6.1) and Clinical Studies (14.3)].] Infusion of approximately 2 hours duration | 600 mg in 500 mL | - Start at 100 mL per hour for the first 15 minutes - Increase to 200 mL per hour for the next 15 minutes - Increase to 250 mL per hour for the next 30 minutes - Increase to 300 mL per hour for the remaining 60 minutes - Duration: 2 hours or longer

2.4 Delayed or Missed Doses

If a planned infusion of OCREVUS is missed, administer OCREVUS as soon as possible; do not wait until the next scheduled dose. Reset the dose schedule to administer the next sequential dose 6 months after the missed dose is administered. Doses of OCREVUS must be separated by at least 5 months [see Dosage and Administration (2.3)].

2.5 Dose Modifications Because of Infusion Reactions

Dose modifications in response to infusion reactions depends on the severity.

Life-threatening Infusion Reactions

Immediately stop and permanently discontinue OCREVUS if there are signs of a life-threatening or disabling infusion reaction [see Warnings and Precautions (5.1)]. Provide appropriate supportive treatment.

Severe Infusion Reactions

Immediately interrupt the infusion and administer appropriate supportive treatment, as necessary [see Warnings and Precautions (5.1)]. Restart the infusion only after all symptoms have resolved. When restarting, begin at half of the infusion rate at the time of onset of the infusion reaction. If this rate is tolerated, increase the rate as described in Table 1 [see Dosage and Administration (2.3)]. This change in rate will increase the total duration of the infusion but not the total dose.

Mild to Moderate Infusion Reactions

Reduce the infusion rate to half the rate at the onset of the infusion reaction and maintain the reduced rate for at least 30 minutes [see Warnings and Precautions (5.1)]. If this rate is tolerated, increase the rate as described in Table 1 [see Dosage and Administration (2.3)]. This change in rate will increase the total duration of the infusion but not the total dose.

2.6 Preparation and Storage of the Dilute Solution for Infusion

Preparation

OCREVUS must be prepared by a healthcare professional using aseptic technique. A sterile needle and syringe should be used to prepare the diluted infusion solution.

Visually inspect for particulate matter and discoloration prior to administration. Do not use the solution if discolored or if the solution contains discrete foreign particulate matter. Do not shake.

Withdraw intended dose and further dilute into an infusion bag containing 0.9% Sodium Chloride Injection, to a final drug concentration of approximately 1.2 mg/mL.

- Withdraw 10 mL (300 mg) of OCREVUS and inject into 250 mL
- Withdraw 20 mL (600 mg) of OCREVUS and inject into 500 mL

Do not use other diluents to dilute OCREVUS since their use has not been tested. The product contains no preservative and is intended for single use only.

Storage of Infusion Solution

Prior to the start of the intravenous infusion, the content of the infusion bag should be at room temperature.

Use the prepared infusion solution immediately. If not used immediately, store up to 24 hours in the refrigerator at 2°C to 8°C (36°F to 46°F) and 8 hours at room temperature up to 25°C (77°F), which includes infusion time. In the event an intravenous infusion cannot be completed the same day, discard the remaining solution.

No incompatibilities between OCREVUS and polyvinyl chloride (PVC) or polyolefin (PO) bags and intravenous (IV) administration sets have been observed.

Administration

Administer the diluted infusion solution through a dedicated line using an infusion set with a 0.2 or 0.22 micron in-line filter.

3 DOSAGE FORMS AND STRENGTHS

Injection: 300 mg/10 mL (30 mg/mL) clear or slightly opalescent, and colorless to pale brown solution in a single-dose vial.

4 CONTRAINDICATIONS

OCREVUS is contraindicated in patients with:

- Active HBV infection [see Dosage and Administration (2.1) and Warnings and Precautions (5.2)]
- A history of life-threatening infusion reaction to OCREVUS [see Warnings and Precautions (5.1)]

5 WARNINGS AND PRECAUTIONS

5.1 Infusion Reactions

OCREVUS can cause infusion reactions, which can include pruritus, rash, urticaria, erythema, bronchospasm, throat irritation, oropharyngeal pain, dyspnea, pharyngeal or laryngeal edema, flushing, hypotension, pyrexia, fatigue, headache, dizziness, nausea, tachycardia, and anaphylaxis. In multiple sclerosis (MS) clinical trials, the incidence of infusion reactions in OCREVUS-treated patients [who received methylprednisolone (or an equivalent steroid) and possibly other pre-medication to reduce the risk of infusion reactions prior to each infusion] was 34 to 40%, with the highest incidence with the first infusion. There were no fatal infusion reactions, but 0.3% of OCREVUS-treated MS patients experienced infusion reactions that were serious, some requiring hospitalization.

Observe patients treated with OCREVUS for infusion reactions during the infusion and for at least one hour after completion of the infusion. Inform patients that infusion reactions can occur up to 24 hours after the infusion.

Reducing the Risk of Infusion Reactions and Managing Infusion Reactions

Administer pre-medication (e.g., methylprednisolone or an equivalent corticosteroid, and an antihistamine) to reduce the frequency and severity of infusion reactions. The addition of an antipyretic (e.g., acetaminophen) may also be considered [see Dosage and Administration (2.2)].

Management recommendations for infusion reactions depend on the type and severity of the reaction [see Dosage and Administration (2.5)]. For life-threatening infusion reactions, immediately and permanently stop OCREVUS and administer appropriate supportive treatment. For less severe infusion reactions, management may involve temporarily stopping the infusion, reducing the infusion rate, and/or administering symptomatic treatment.

5.2 Infections

Serious, including life-threatening or fatal, bacterial, viral, parasitic and fungal infections have been reported in patients receiving OCREVUS. An increased risk of infections (including serious and fatal bacterial, fungal, and new or reactivated viral infections) has been observed in patients during and following completion of treatment with anti-CD20 B-cell depleting therapies.

A higher proportion of OCREVUS-treated patients experienced infections compared to patients taking REBIF or placebo. In RMS trials, 58% of OCREVUS-treated patients experienced one or more infections compared to 52% of REBIF-treated patients. In the PPMS trial, 70% of OCREVUS-treated patients experienced one or more infections compared to 68% of patients on placebo. OCREVUS increased the risk for upper respiratory tract infections, lower respiratory tract infections, skin infections, and herpes-related infections [see Adverse Reactions (6.1)].

OCREVUS was not associated with an increased risk of serious infections in MS patients in controlled trials.

Delay OCREVUS administration in patients with an active infection until the infection is resolved.

Respiratory Tract Infections

A higher proportion of OCREVUS-treated patients experienced respiratory tract infections compared to patients taking REBIF or placebo. In RMS trials, 40% of OCREVUS-treated patients experienced upper respiratory tract infections compared to 33% of REBIF-treated patients, and 8% of OCREVUS-treated patients experienced lower respiratory tract infections compared to 5% of REBIF-treated patients. In the PPMS trial, 49% of OCREVUS-treated patients experienced upper respiratory tract infections compared to 43% of patients on placebo and 10% of OCREVUS-treated patients experienced lower respiratory tract infections compared to 9% of patients on placebo. The infections were predominantly mild to moderate and consisted mostly of upper respiratory tract infections and bronchitis.

Herpes

In active-controlled (RMS) clinical trials, herpes infections were reported more frequently in OCREVUS-treated patients than in REBIF-treated patients, including herpes zoster (2.1% vs. 1.0%), herpes simplex (0.7% vs. 0.1%), oral herpes (3.0% vs. 2.2%), genital herpes (0.1% vs. 0%), and herpes virus infection (0.1% vs. 0%). Infections were predominantly mild to moderate in severity.

In the placebo-controlled (PPMS) clinical trial, oral herpes was reported more frequently in the OCREVUS-treated patients than in the patients on placebo (2.7% vs 0.8%).

Serious cases of infections caused by herpes simplex virus and varicella zoster virus, including central nervous system infections (encephalitis and meningitis), intraocular infections, and disseminated skin and soft tissue infections, have been reported in the postmarketing setting in multiple sclerosis patients receiving OCREVUS. Serious herpes virus infections may occur at any time during treatment with OCREVUS. Some cases were life-threatening.

If serious herpes infections occur, OCREVUS should be discontinued or withheld until the infection has resolved, and appropriate treatment should be administered [see Patient Counseling Information (17)].

Hepatitis B Virus (HBV) Reactivation

Hepatitis B reactivation has been reported in MS patients treated with OCREVUS in the postmarketing setting. Fulminant hepatitis, hepatic failure, and death caused by HBV reactivation have occurred in patients treated with anti-CD20 antibodies. Perform HBV screening in all patients before initiation of treatment with OCREVUS. Do not administer OCREVUS to patients with active HBV confirmed by positive results for HBsAg and anti-HB tests. For patients who are negative for surface antigen [HBsAg] and positive for HB core antibody [HBcAb+] or are carriers of HBV [HBsAg+], consult liver disease experts before starting and during treatment.

Possible Increased Risk of Immunosuppressant Effects with Other Immunosuppressants

When initiating OCREVUS after an immunosuppressive therapy or initiating an immunosuppressive therapy after OCREVUS, consider the potential for increased immunosuppressive effects [see Drug Interactions (7.1) and Clinical Pharmacology (12.1, 12.2)]. OCREVUS has not been studied in combination with other MS therapies.

Vaccinations

Administer all immunizations according to immunization guidelines at least 4 weeks prior to initiation of OCREVUS for live or live-attenuated vaccines and, whenever possible, at least 2 weeks prior to initiation of OCREVUS for non-live vaccines.

OCREVUS may interfere with the effectiveness of non-live vaccines [see Drug Interactions (7.2)].

The safety of immunization with live or live-attenuated vaccines following OCREVUS therapy has not been studied, and vaccination with live-attenuated or live vaccines is not recommended during treatment and until B-cell repletion [see Clinical Pharmacology (12.2)].

Vaccination of Infants Born to Mothers Treated with OCREVUS During Pregnancy

In infants of mothers exposed to OCREVUS during pregnancy, do not administer live or live-attenuated vaccines before confirming the recovery of B-cell counts as measured by CD19^+ B-cells. Depletion of B-cells in these infants may increase the risks from live or live-attenuated vaccines.

You may administer non-live vaccines, as indicated, prior to recovery from B-cell depletion, but should consider assessing vaccine immune responses, including consultation with a qualified specialist, to assess whether a protective immune response was mounted [see Use in Specific Populations (8.1)].

5.3 Progressive Multifocal Leukoencephalopathy (PML)

Cases of progressive multifocal leukoencephalopathy (PML) have been reported in patients with MS treated with OCREVUS in the postmarketing setting. PML is an opportunistic viral infection of the brain caused by the JC virus (JCV) that typically only occurs in patients who are immunocompromised, and that usually leads to death or severe disability. PML has occurred in OCREVUS-treated patients who had not been treated previously with natalizumab (which has a known association with PML), were not taking any immunosuppressive or immunomodulatory medications associated with the risk of PML prior to or concomitantly with OCREVUS, and did not have any known ongoing systemic medical conditions resulting in compromised immune system function.

JCV infection resulting in PML has also been observed in patients treated with other anti-CD20 antibodies and other MS therapies.

At the first sign or symptom suggestive of PML, withhold OCREVUS and perform an appropriate diagnostic evaluation. Typical symptoms associated with PML are diverse, progress over days to weeks, and include progressive weakness on one side of the body or clumsiness of limbs, disturbance of vision, and changes in thinking, memory, and orientation leading to confusion and personality changes.

MRI findings may be apparent before clinical signs or symptoms. Cases of PML, diagnosed based on MRI findings and the detection of JCV DNA in the cerebrospinal fluid in the absence of clinical signs or symptoms specific to PML, have been reported in patients treated with other MS medications associated with PML. Many of these patients subsequently became symptomatic with PML. Therefore, monitoring with MRI for signs that may be consistent with PML may be useful, and any suspicious findings should lead to further investigation to allow for an early diagnosis of PML, if present. Following discontinuation of another MS medication associated with PML, lower PML-related mortality and morbidity have been reported in patients who were initially asymptomatic at diagnosis compared to patients who had characteristic clinical signs and symptoms at diagnosis.

It is not known whether these differences are due to early detection and discontinuation of MS treatment or due to differences in disease in these patients.

If PML is confirmed, treatment with OCREVUS should be discontinued.

5.4 Reduction in Immunoglobulins

As expected with any B-cell depleting therapy, decreased immunoglobulin levels are observed with OCREVUS treatment. The pooled data of OCREVUS clinical studies (RMS and PPMS) and their open-label extensions (up to approximately 7 years of exposure) have shown an association between decreased levels of immunoglobulin G (IgG<LLN) and increased rates of serious infections. Monitor the levels of quantitative serum immunoglobulins during OCREVUS treatment and after discontinuation of treatment, until B-cell repletion, and especially in the setting of recurrent serious infections. Consider discontinuing OCREVUS therapy in patients with serious opportunistic or recurrent serious infections, and if prolonged hypogammaglobulinemia requires treatment with intravenous immunoglobulins [see Adverse Reactions (6.1)].

5.5 Malignancies

An increased risk of malignancy with OCREVUS may exist. In controlled trials, malignancies, including breast cancer, occurred more frequently in OCREVUS-treated patients. Breast cancer occurred in 6 of 781 females treated with OCREVUS and none of 668 females treated with REBIF or placebo. Patients should follow standard breast cancer screening guidelines.

5.6 Immune-Mediated Colitis

Immune-mediated colitis, which can present as a severe and acute-onset form of colitis, has been reported in patients receiving OCREVUS in the postmarketing setting. Some cases of colitis were serious, requiring hospitalization, with a few patients requiring surgical intervention. Systemic corticosteroids were required in many of these patients. The time from treatment initiation to onset of symptoms in these cases ranged from a few weeks to years. Monitor patients for immune-mediated colitis during OCREVUS treatment, and evaluate promptly if signs and symptoms that may indicate immune-mediated colitis, such as new or persistent diarrhea or other gastrointestinal signs and symptoms, occur.

5.7 Liver Injury

Clinically significant liver injury, without findings of viral hepatitis, has been reported in the postmarketing setting in patients treated with anti-CD20 B-cell depleting therapies approved for the treatment of MS, including OCREVUS. Signs of liver injury, including markedly elevated serum hepatic enzymes with elevated total bilirubin, have occurred from weeks to months after administration.

Patients treated with OCREVUS found to have an alanine aminotransferase (ALT) or aspartate aminotransferase (AST) greater than 3× the upper limit of normal (ULN) with serum total bilirubin greater than 2× ULN are potentially at risk for severe drug-induced liver injury.

Obtain liver function tests prior to initiating treatment with OCREVUS [see Dosage and Administration (2.1)], and monitor for signs and symptoms of any hepatic injury during treatment. Measure serum aminotransferases, alkaline phosphatase, and bilirubin levels promptly in patients who report symptoms that may indicate liver injury, including new or worsening fatigue, anorexia, nausea, vomiting, right upper abdominal discomfort, dark urine, or jaundice. If liver injury is present and an alternative etiology is not identified, discontinue OCREVUS.

6 ADVERSE REACTIONS

The following serious adverse reactions are discussed in greater detail in other sections of the labeling:

- Infusion Reactions [see Warnings and Precautions (5.1)]
- Infections [see Warnings and Precautions (5.2)]
- Progressive Multifocal Leukoencephalopathy [see Warnings and Precautions (5.3)]
- Reduction in Immunoglobulins [see Warnings and Precautions (5.4)]
- Malignancies [see Warnings and Precautions (5.5)]
- Immune-Mediated Colitis [see Warnings and Precautions (5.6)]
- Liver Injury [see Warnings and Precautions (5.7)]

6.1 Clinical Trials Experience

Because clinical trials are conducted under widely varying conditions, adverse reactions rates observed in the clinical trials of a drug cannot be directly compared to rates in the clinical trials of another drug and may not reflect the rates observed in clinical practice.

The safety of OCREVUS has been evaluated in 1311 patients across MS clinical studies, which included 825 patients in active-controlled clinical trials in patients with relapsing forms of MS (RMS) and 486 patients in a placebo-controlled study in patients with primary progressive MS (PPMS).

Adverse Reactions in Patients with Relapsing Forms of MS

In active-controlled clinical trials (Study 1 and Study 2), 825 patients with RMS received OCREVUS 600 mg intravenously every 24 weeks (initial treatment was given as two separate 300 mg infusions at Weeks 0 and 2) [see Clinical Studies (14.1)]. The overall exposure in the 96-week controlled treatment periods was 1448 patient-years.

The most common adverse reactions in RMS trials (incidence ≥ 10%) were upper respiratory tract infections and infusion reactions. Table 2 summarizes the adverse reactions that occurred in RMS trials (Study 1 and Study 2).

Table 2 Adverse Reactions in Adult Patients with RMS with an Incidence of at least 5% for OCREVUS and Higher than REBIF
Adverse Reactions | Studies 1 and 2
Adverse Reactions | OCREVUS 600 mg IV Every 24 Weeks [The first dose was given as two separate 300 mg infusions at Weeks 0 and 2.] (n=825) % | REBIF 44 mcg SQ 3 Times per Week (n=826) %
Upper respiratory tract infections | 40 | 33
Infusion reactions | 34 | 10
Depression | 8 | 7
Lower respiratory tract infections | 8 | 5
Back pain | 6 | 5
Herpes virus- associated infections | 6 | 4
Pain in extremity | 5 | 4

Adverse Reactions in Patients with Primary Progressive MS

In a placebo-controlled clinical trial (Study 3), a total of 486 patients with PPMS received one course of OCREVUS (600 mg of OCREVUS administered as two 300 mg infusions two weeks apart) given intravenously every 24 weeks and 239 patients received placebo intravenously [see Clinical Studies (14.2)]. The overall exposure in the controlled treatment period was 1416 patient-years, with median treatment duration of 3 years.

The most common adverse reactions in the PPMS trial (incidence ≥ 10%) were upper respiratory tract infections, infusion reactions, skin infections, and lower respiratory tract infections. Table 3 summarizes the adverse reactions that occurred in the PPMS trial (Study 3).

Table 3 Adverse Reactions in Adult Patients with PPMS with an Incidence of at least 5% for OCREVUS and Higher than Placebo
Adverse Reactions | Study 3
Adverse Reactions | OCREVUS 600 mg IV Every 24 Weeks [One dose of OCREVUS (600 mg administered as two 300 mg infusions two weeks apart)] | Placebo
Adverse Reactions | (n=486) % | (n=239) %
Upper respiratory tract infections | 49 | 43
Infusion reactions | 40 | 26
Skin infections | 14 | 11
Lower respiratory tract infections | 10 | 9
Cough | 7 | 3
Diarrhea | 6 | 5
Edema peripheral | 6 | 5
Herpes virus associated infections | 5 | 4

Adverse Reactions in Patients who Received 2-hour Infusions

Study 4 was designed to characterize the safety profile of OCREVUS infusions administered over 2 hours in patients with Relapsing-Remitting Multiple Sclerosis who did not experience a serious infusion reaction with any previous OCREVUS infusion. In this study, the incidence, intensity, and types of symptoms of infusion reactions were consistent with those of infusions administered over 3.5 hours [see Clinical Studies (14.3)].

Laboratory Abnormalities

Decreased Immunoglobulins

OCREVUS decreased total immunoglobulins with the greatest decline seen in IgM levels; however, a decrease in IgG levels was associated with an increased rate of serious infections.

In the active-controlled (RMS) trials (Study 1 and Study 2), the proportion of patients at baseline reporting IgG, IgA, and IgM below the lower limit of normal (LLN) in OCREVUS-treated patients was 0.5%, 1.5%, and 0.1%, respectively. Following treatment, the proportion of OCREVUS-treated patients reporting IgG, IgA, and IgM below the LLN at 96 weeks was 1.5%, 2.4%, and 16.5%, respectively.

In the placebo-controlled (PPMS) trial (Study 3), the proportion of patients at baseline reporting IgG, IgA, and IgM below the LLN in OCREVUS-treated patients was 0.0%, 0.2%, and 0.2%, respectively. Following treatment, the proportion of OCREVUS-treated patients reporting IgG, IgA, and IgM below the LLN at 120 weeks was 1.1%, 0.5%, and 15.5%, respectively.

The pooled data of OCREVUS clinical studies (RMS and PPMS) and their open-label extensions (up to approximately 7 years of exposure) have shown an association between decreased levels of IgG and increased rates of serious infections. The type, severity, latency, duration, and outcome of serious infections observed during episodes of immunoglobulins below LLN were consistent with the overall serious infections observed in patients treated with OCREVUS.

Decreased Neutrophil Levels

In the PPMS clinical trial (Study 3), decreased neutrophil counts occurred in 13% of OCREVUS-treated patients compared to 10% in placebo patients. The majority of the decreased neutrophil counts were only observed once for a given patient treated with OCREVUS and were between LLN - 1.5 × 10^9/L and 1.0 × 10^9/L. Overall, 1% of the patients in the OCREVUS group had neutrophil counts less than 1.0 × 10^9/L and these were not associated with an infection.

6.2 Immunogenicity

As with all therapeutic proteins, there is potential for immunogenicity. Immunogenicity data are highly dependent on the sensitivity and specificity of the test methods used. Additionally, the observed incidence of a positive result in a test method may be influenced by several factors, including sample handling, timing of sample collection, drug interference, concomitant medication, and the underlying disease. Therefore, comparison of the incidence of antibodies to OCREVUS with the incidence of antibodies to other products may be misleading.

Patients in MS trials (Study 1, Study 2, and Study 3) were tested at multiple time points (baseline and every 6 months post-treatment for the duration of the trial) for anti-drug antibodies (ADAs). Out of 1311 patients treated with OCREVUS, 12 (~1%) tested positive for ADAs, of which 2 patients tested positive for neutralizing antibodies. These data are not adequate to assess the impact of ADAs on the safety and efficacy of OCREVUS.

6.3 Postmarketing Experience

The following adverse reactions have been identified during postapproval use of OCREVUS. Because these reactions are reported voluntarily from a population of uncertain size, it is not always possible to reliably estimate their frequency or establish a causal relationship to drug exposure.

Gastrointestinal Disorders: Immune-mediated colitis [see Warnings and Precautions (5.6)]

Hepatobiliary Disorders: Liver injury [see Warnings and Precautions (5.7)]

Infections and Infestations: Serious herpes infections [see Warnings and Precautions (5.2)], progressive multifocal leukoencephalopathy [see Warnings and Precautions (5.3)], and babesiosis

Skin: Pyoderma gangrenosum

7 DRUG INTERACTIONS

7.1 Immunosuppressive or Immune-Modulating Therapies

The concomitant use of OCREVUS and other immune-modulating or immunosuppressive therapies, including immunosuppressant doses of corticosteroids, is expected to increase the risk of immunosuppression. Consider the risk of additive immune system effects when coadministering immunosuppressive therapies with OCREVUS. When switching from drugs with prolonged immune effects, such as daclizumab, fingolimod, natalizumab, teriflunomide, or mitoxantrone, consider the duration and mode of action of these drugs because of additive immunosuppressive effects when initiating OCREVUS [see Warnings and Precautions (5.2)].

7.2 Vaccinations

A Phase 3b randomized, open-label study examined the concomitant use of OCREVUS and several non-live vaccines in adults 18-55 years of age with relapsing forms of MS (68 subjects undergoing treatment with OCREVUS at the time of vaccination and 34 subjects not undergoing treatment with OCREVUS at the time of vaccination). Concomitant exposure to OCREVUS attenuated antibody responses to tetanus toxoid-containing vaccine, pneumococcal polysaccharide, pneumococcal conjugate vaccines, and seasonal inactivated influenza vaccines. The impact of the observed attenuation on vaccine effectiveness in this patient population is unknown. The safety and effectiveness of live or live-attenuated vaccines administered concomitantly with OCREVUS have not been assessed [see Warnings and Precautions (5.2)].

8 USE IN SPECIFIC POPULATIONS

8.1 Pregnancy

Risk Summary

OCREVUS is a humanized monoclonal antibody of an immunoglobulin G1 subtype and immunoglobulins are known to cross the placental barrier. There are no adequate data on the developmental risk associated with use of OCREVUS in pregnant women. However, transient peripheral B-cell depletion and lymphocytopenia have been reported in infants born to mothers exposed to other anti-CD20 antibodies during pregnancy. B-cell levels in infants following maternal exposure to OCREVUS have not been studied in clinical trials. The potential duration of B-cell depletion in such infants, and the impact of B-cell depletion on vaccine safety and effectiveness, is unknown [see Warnings and Precautions (5.2)].

Following administration of ocrelizumab to pregnant monkeys at doses similar to or greater than those used clinically, increased perinatal mortality, depletion of B-cell populations, renal, bone marrow, and testicular toxicity were observed in the offspring in the absence of maternal toxicity [see Data].

In the U.S. general population, the estimated background risk of major birth defects and miscarriage in clinically recognized pregnancies is 2% to 4% and 15% to 20%, respectively. The background risk of major birth defects and miscarriage for the indicated population is unknown.

Data

Animal Data

Following intravenous administration of OCREVUS to monkeys during organogenesis (loading doses of 15 or 75 mg/kg on gestation days 20, 21, and 22, followed by weekly doses of 20 or 100 mg/kg), depletion of B-lymphocytes in lymphoid tissue (spleen and lymph nodes) was observed in fetuses at both doses.

Intravenous administration of OCREVUS (three daily loading doses of 15 or 75 mg/kg, followed by weekly doses of 20 or 100 mg/kg) to pregnant monkeys throughout the period of organogenesis and continuing through the neonatal period resulted in perinatal deaths (some associated with bacterial infections), renal toxicity (glomerulopathy and inflammation), lymphoid follicle formation in the bone marrow, and severe decreases in circulating B-lymphocytes in neonates. The cause of the neonatal deaths is uncertain; however, both affected neonates were found to have bacterial infections. Reduced testicular weight was observed in neonates at the high dose.

A no-effect dose for adverse developmental effects was not identified; the doses tested in monkey are 2 and 10 times the recommended human dose of 600 mg, on a mg/kg basis.

8.2 Lactation

Risk Summary

There are no data on the presence of ocrelizumab in human milk, the effects on the breastfed infant, or the effects of the drug on milk production. Ocrelizumab was excreted in the milk of ocrelizumab-treated monkeys. Human IgG is excreted in human milk, and the potential for absorption of ocrelizumab to lead to B-cell depletion in the infant is unknown. The developmental and health benefits of breastfeeding should be considered along with the mother's clinical need for OCREVUS and any potential adverse effects on the breastfed infant from OCREVUS or from the underlying maternal condition.

8.3 Females and Males of Reproductive Potential

Contraception

Women of childbearing potential should use effective contraception while receiving OCREVUS and for 6 months after the last infusion of OCREVUS [see Clinical Pharmacology (12.3)].

8.4 Pediatric Use

Safety and effectiveness of OCREVUS in pediatric patients have not been established.

8.5 Geriatric Use

Clinical studies of OCREVUS did not include sufficient numbers of subjects aged 65 and over to determine whether they respond differently from younger subjects.

11 DESCRIPTION

Ocrelizumab is a recombinant humanized monoclonal antibody directed against CD20-expressing B-cells. Ocrelizumab is a glycosylated immunoglobulin G1 (IgG1) with a molecular mass of approximately 145 kDa.

OCREVUS (ocrelizumab) injection for intravenous infusion is a preservative-free, sterile, clear or slightly opalescent, and colorless to pale brown solution supplied in single-dose vials. Each mL of solution contains 30 mg ocrelizumab, glacial acetic acid (0.25 mg), polysorbate 20 (0.2 mg), sodium acetate trihydrate (2.14 mg), and trehalose dihydrate (40 mg) at pH 5.3.

12 CLINICAL PHARMACOLOGY

12.1 Mechanism of Action

The precise mechanism by which ocrelizumab exerts its therapeutic effects in multiple sclerosis is unknown, but is presumed to involve binding to CD20, a cell surface antigen present on pre-B and mature B lymphocytes. Following cell surface binding to B lymphocytes, ocrelizumab results in antibody-dependent cellular cytolysis and complement-mediated lysis.

12.2 Pharmacodynamics

For B-cell counts, assays for CD19^+ B-cells are used because the presence of OCREVUS interferes with the CD20 assay. Treatment with OCREVUS reduces CD19^+ B-cell counts in blood by 14 days after infusion. In clinical studies, B-cell counts rose to above the lower limit of normal (LLN) or above baseline counts between infusions of OCREVUS at least one time in 0.3% to 4.1% of patients. In a clinical study of 51 patients, the median time for B-cell counts to return to either baseline or LLN was 72 weeks (range 27-175 weeks) after the last OCREVUS infusion. Within 2.5 years after the last infusion, B-cell counts rose to either baseline or LLN in 90% of patients.

12.3 Pharmacokinetics

Pharmacokinetics (PK) of OCREVUS in MS clinical studies fit a two compartment model with time-dependent clearance. The overall exposure at the steady-state (AUC over the 24 week dosing intervals) of OCREVUS was 3,510 mcg/mL per day. In clinical studies in MS patients, maintenance doses of ocrelizumab were either 600 mg every 6 months (RMS patients) or two 300 mg infusions separated by 14 days every 6 months (PPMS patients). The mean maximum concentration was 212 mcg/mL in patients with RMS (600 mg infusion over 3.5 hours) and 141 mcg/mL in patients with PPMS (two 300 mg infusions over 2.5 hours administered within two weeks). The mean maximum peak concentrations (Cmax) of ocrelizumab in patients with relapsing-remitting multiple sclerosis (RRMS) observed after the 3.5-hour infusion and 2-hour infusion were 202 ± 42 (mean ± SD) and 200 ± 46 mcg/mL, respectively, compared to the previously reported Cmax of 212 mcg/mL. The pharmacokinetics of ocrelizumab was essentially linear and dose proportional between 400 mg and 2000 mg.

Distribution

The population PK estimate of the central volume of distribution was 2.78 L. Peripheral volume and inter-compartment clearance were estimated at 2.68 L and 0.29 L/day, respectively.

Elimination

Constant clearance was estimated at 0.17 L/day, and initial time-dependent clearance at 0.05 L/day, which declined with a half-life of 33 weeks. The terminal elimination half-life was 26 days.

Metabolism

The metabolism of OCREVUS has not been directly studied because antibodies are cleared principally by catabolism.

Specific Populations

Renal Impairment

Patients with mild renal impairment were included in clinical trials. No significant change in the pharmacokinetics of OCREVUS was observed in those patients.

Hepatic Impairment

Patients with mild hepatic impairment were included in clinical trials. No significant change in the pharmacokinetics of OCREVUS was observed in those patients.

13 NONCLINICAL TOXICOLOGY

13.1 Carcinogenesis, Mutagenesis, Impairment of Fertility

No carcinogenicity studies have been performed to assess the carcinogenic potential of OCREVUS.

No studies have been performed to assess the mutagenic potential of OCREVUS. As an antibody, OCREVUS is not expected to interact directly with DNA.

No effects on reproductive organs were observed in male monkeys administered ocrelizumab by intravenous injection (three loading doses of 15 or 75 mg/kg, followed by weekly doses of 20 or 100 mg/kg) for 8 weeks. There were also no effects on estrus cycle in female monkeys administered ocrelizumab over three menstrual cycles using the same dosing regimen. The doses tested in monkey are 2 and 10 times the recommended human dose of 600 mg, on a mg/kg basis.

14 CLINICAL STUDIES

14.1 Relapsing Forms of Multiple Sclerosis (RMS)

The efficacy of OCREVUS was demonstrated in two randomized, double-blind, double-dummy, active comparator-controlled clinical trials of identical design, in patients with RMS treated for 96 weeks (Study 1 and Study 2). The dose of OCREVUS was 600 mg every 24 weeks (initial treatment was given as two 300 mg IV infusions administered 2 weeks apart, and subsequent doses were administered as a single 600 mg IV infusion) and placebo subcutaneous injections were given 3 times per week. The dose of REBIF, the active comparator, was 44 mcg given as subcutaneous injections 3 times per week and placebo IV infusions were given every 24 weeks. Both studies included patients who had experienced at least one relapse within the prior year, or two relapses within the prior two years, and had an Expanded Disability Status Scale (EDSS) score from 0 to 5.5. Patients with primary progressive forms of multiple sclerosis (MS) were excluded. Neurological evaluations were performed every 12 weeks and at the time of a suspected relapse. Brain MRIs were performed at baseline and at Weeks 24, 48, and 96.

The primary outcome of both Study 1 and Study 2 was the annualized relapse rate (ARR). Additional outcome measures included the proportion of patients with confirmed disability progression, the mean number of MRI T1 gadolinium (Gd)-enhancing lesions at Weeks 24, 48, and 96, and new or enlarging MRI T2 hyperintense lesions. Progression of disability was defined as an increase of 1 point or more from the baseline EDSS score attributable to MS when the baseline EDSS score was 5.5 or less, or 0.5 points or more when the baseline EDSS score was above 5.5. Disability progression was considered confirmed when the increase in the EDSS was confirmed at a regularly scheduled visit 12 weeks after the initial documentation of neurological worsening. The primary population for analysis of confirmed disability progression was the pooled population from Studies 1 and 2.

In Study 1, 410 patients were randomized to OCREVUS and 411 to REBIF; 11% of OCREVUS-treated and 17% of REBIF-treated patients did not complete the 96-week double-blind treatment period. The baseline demographic and disease characteristics were balanced between the two treatment groups. At baseline, the mean age of patients was 37 years; 66% were female. The mean time from MS diagnosis to randomization was 3.8 years, the mean number of relapses in the previous year was 1.3, and the mean EDSS score was 2.8; 74% of patients had not been treated with a non-steroid therapy for MS in the 2 years prior to the study. At baseline, 40% of patients had one or more T1 Gd-enhancing lesions (mean 1.8).

In Study 2, 417 patients were randomized to OCREVUS and 418 to REBIF; 14% of OCREVUS-treated and 23% of REBIF-treated patients did not complete the 96-week double-blind treatment period. The baseline demographic and disease characteristics were balanced between the two treatment groups. At baseline, the mean age of patients was 37 years; 66% were female. The mean time from MS diagnosis to randomization was 4.1 years, the mean number of relapses in the previous year was 1.3, and the mean EDSS score was 2.8; 74% of patients had not been treated with a non-steroid therapy for MS in the 2 years prior to the study. At baseline, 40% of OCREVUS-treated patients had one or more T1 Gd-enhancing lesions (mean 1.9).

In Study 1 and Study 2, OCREVUS significantly lowered the annualized relapse rate and the proportion of patients with disability progression confirmed at 12 weeks after onset compared to REBIF. Results for Study 1 and Study 2 are presented in Table 4 and Figure 1.

Table 4 Key Clinical and MRI Endpoints in RMS Patients from Study 1 and Study 2
Endpoints | Study 1 |  | Study 2
Endpoints | OCREVUS 600 mg every 24 weeks | REBIF 44 mcg three times a week | OCREVUS 600 mg every 24 weeks | REBIF 44 mcg three times a week
Endpoints | N=410 | N=411 | N=417 | N=418
Clinical Endpoints
Annualized Relapse Rate (Primary Endpoint) | 0.156 | 0.292 | 0.155 | 0.290
Relative Reduction | 46% (p<0.0001) |  | 47% (p<0.0001)
Proportion Relapse-free | 83% | 71% | 82% | 72%
Proportion of Patients with 12-week Confirmed Disability Progression [Defined as an increase of 1.0 point or more from the baseline Expanded Disability Status Scale (EDSS) score for patients with baseline score of 5.5 or less, or 0.5 or more when the baseline score is greater than 5.5, Kaplan-Meier estimates at Week 96.] | 9.8% OCREVUS vs 15.2% REBIF
Risk Reduction (Pooled Analysis [Data prospectively pooled from Study 1 and Study 2.]) | 40%; p=0.0006
MRI Endpoints
Mean number of T1 Gd-enhancing lesions per MRI scan | 0.016 | 0.286 | 0.021 | 0.416
Relative Reduction | 94% (p<0.0001) |  | 95% (p<0.0001)
Mean number of new and/or enlarging T2 hyperintense lesions per MRI | 0.323 | 1.413 | 0.325 | 1.904
Relative Reduction | 77% (p<0.0001) |  | 83% (p<0.0001)

Figure 1 Kaplan-Meier Plot [Pre-specified pooled analysis of Study 1 and 2] of Time to Onset of Confirmed Disability Progression Sustained for at Least 12 Weeks with the Initial Event of Neurological Worsening Occurring During the Double-blind Treatment Period in Pooled Studies 1 and 2 in Patients with RMS (Pooled ITT Population)

In exploratory subgroup analyses of Study 1 and Study 2, the effect of OCREVUS on annualized relapse rate and disability progression was similar in male and female patients.

14.2 Primary Progressive Multiple Sclerosis (PPMS)

Study 3 was a randomized, double-blind, placebo-controlled clinical trial in patients with PPMS. Patients were randomized 2:1 to receive either OCREVUS 600 mg or placebo as two 300 mg intravenous infusions 2 weeks apart every 24 weeks for at least 120 weeks. Selection criteria required a baseline EDSS of 3 to 6.5 and a score of 2 or greater for the EDSS pyramidal functional system due to lower extremity findings. Neurological assessments were conducted every 12 weeks. An MRI scan was obtained at baseline and at Weeks 24, 48, and 120.

In Study 3, the primary outcome was the time to onset of disability progression attributable to MS confirmed to be present at the next neurological assessment at least 12 weeks later. Disability progression occurred when the EDSS score increased by 1 point or more from the baseline EDSS if the baseline EDSS was 5.5 points or less, or by 0.5 points or more if the baseline EDSS was more than 5.5 points. In Study 3, confirmed disability progression also was deemed to have occurred if patients who had onset of disability progression discontinued participation in the study before the next assessment. Additional outcome measures included timed 25-foot walk, and percentage change in T2 hyperintense lesion volume.

Study 3 randomized 488 patients to OCREVUS and 244 to placebo; 21% of OCREVUS-treated patients and 34% of placebo-treated patients did not complete the trial. The baseline demographic and disease characteristics were balanced between the two treatment groups. At baseline, the mean age of patients was 45; 49% were female. The mean time since symptom onset was 6.7 years, the mean EDSS score was 4.7, and 26% had one or more T1 Gd-enhancing lesions at baseline; 88% of patients had not been treated previously with a non-steroid treatment for MS. The time to onset of disability progression confirmed at 12 weeks after onset was significantly longer for OCREVUS-treated patients than for placebo-treated patients (see Figure 2). Results for Study 3 are presented in Table 5 and Figure 2.

Table 5 Key Clinical and MRI Endpoints in PPMS Patients for Study 3
Endpoints | Study 3
Endpoints | OCREVUS 600 mg (two 300 mg infusions two weeks apart every 24 weeks) | Placebo
Endpoints | N=488 | N=244
Clinical Outcomes
Proportion of patients with 12-week Confirmed Disability Progression [Defined as an increase of 1.0 point or more from the baseline EDSS score for patients with baseline score of 5.5 or less, or an increase of 0.5 or more when the baseline score is more than 5.5] | 32.9% | 39.3%
Risk reduction | 24%; p=0.0321
MRI Endpoints
Mean change in volume of T2 lesions, from baseline to Week 120 (cm^3) | -0.39 | 0.79
Mean change in volume of T2 lesions, from baseline to Week 120 (cm^3) | p<0.0001

Figure 2 Kaplan-Meier Plot of Time to Onset of Confirmed Disability Progression Sustained for at Least 12 Weeks with the Initial Event of Neurological Worsening Occurring During the Double-blind Treatment Period in Study 3 [All patients in this analysis had a minimum of 120 weeks of follow-up. The primary analysis is based on all disability progression events accrued including 21 without confirmatory EDSS at 12 weeks.]

In the overall population in Study 3, the proportion of patients with 20 percent worsening of the timed 25-foot walk confirmed at 12 weeks was 49% in OCREVUS-treated patients compared to 59% in placebo-treated patients (25% risk reduction).

In exploratory subgroup analyses of Study 3, the proportion of female patients with disability progression confirmed at 12 weeks after onset was similar in OCREVUS-treated patients and placebo-treated patients (approximately 36% in each group). In male patients, the proportion of patients with disability progression confirmed at 12 weeks after onset was approximately 30% in OCREVUS-treated patients and 43% in placebo-treated patients. Clinical and MRI endpoints that generally favored OCREVUS numerically in the overall population, and that showed similar trends in both male and female patients, included annualized relapse rate, change in T2 lesion volume, and number of new or enlarging T2 lesions.

14.3 Safety Study of 2-Hour Infusions

The safety of the 2-hour OCREVUS infusion was evaluated in Study 4 (NCT03085810), a prospective, multicenter, randomized, double-blind, controlled, parallel arm substudy in patients with Relapsing-Remitting Multiple Sclerosis who were naïve to other non-steroid therapies for MS and did not experience a serious infusion reaction with any previous OCREVUS infusion. The first dose of OCREVUS was administered as two 300 mg infusions (600 mg total) separated by 14 days. After enrollment in the substudy, patients were randomized in a 1:1 ratio to receive infusions over approximately 3.5-hours or 2-hours, after appropriate premedication [see Dosage and Administration (2.2)], every 24 weeks. The randomization was stratified by region and the dose at which patients were first randomized.

The primary endpoint of the substudy was the proportion of patients with infusion reactions occurring during or within 24 hours following the first randomized infusion of OCREVUS. The primary analysis was performed when 580 patients were randomized, at which time 469/579 (81%) of the treated patients had received only a single randomized infusion of OCREVUS. The proportions of patients with infusion reactions occurring during or within 24 hours following the first randomized infusion in this substudy were similar between the 2-hour and 3.5-hour infusion groups (24.4% versus 23.3%, respectively). Overall, in all randomized doses, 27.1% of the patients in the 2-hour infusion group and 25.0% of the patients in the 3.5-hour infusion group reported mild or moderate infusion reactions; two infusion reactions were severe in intensity, with one severe infusion reaction (0.3%) reported in one patient in each group in this substudy [see Warnings and Precautions (5.1)]. There were no life-threatening, fatal, or serious infusion reactions in this substudy.

16 HOW SUPPLIED/STORAGE AND HANDLING

OCREVUS (ocrelizumab) injection is a preservative-free, sterile, clear or slightly opalescent, and colorless to pale brown solution supplied as a carton containing one 300 mg/10 mL (30 mg/mL) single-dose vial (NDC 50242-150-01).

STORAGE AND HANDLING

Store OCREVUS vials at 2°C to 8°C (36°F to 46°F) in the outer carton to protect from light. Do not freeze or shake.

17 PATIENT COUNSELING INFORMATION

Advise the patient to read the FDA-approved patient labeling (Medication Guide).

Infusion Reactions

Inform patients about the signs and symptoms of infusion reactions, and that infusion reactions can occur up to 24 hours after infusion. Advise patients to contact their healthcare provider immediately for signs or symptoms of infusion reactions [see Warnings and Precautions (5.1)].

Infection

Advise patients to contact their healthcare provider for any signs of infection during treatment or after the last dose [see Clinical Pharmacology (12.2)]. Signs include fever, chills, constant cough, dysuria, or signs of herpes such as cold sores, shingles, or genital sores [see Warnings and Precautions (5.2)].

Advise patients that OCREVUS may cause reactivation of hepatitis B infection and that monitoring will be required if they are at risk [see Warnings and Precautions (5.2)].

Advise patients that herpes infections, including serious herpes infections affecting the central nervous system, skin, and eyes, have occurred during treatment with OCREVUS. Advise patients to promptly contact their healthcare provider if they experience any signs or symptoms of herpes infections including oral or genital symptoms, fever, skin rash, pain, itching, decreased visual acuity, eye redness, eye pain, headache, neck stiffness, or change in mental status [see Warnings and Precautions (5.2)].

Vaccination

Advise patients to complete any required live or live-attenuated vaccinations at least 4 weeks and, whenever possible, non-live vaccinations at least 2 weeks prior to initiation of OCREVUS. Administration of live-attenuated or live vaccines is not recommended during OCREVUS treatment and until B-cell recovery [see Warnings and Precautions (5.2)].

Progressive Multifocal Leukoencephalopathy

Inform patients that PML has occurred in patients who received OCREVUS. Inform the patient that PML is characterized by a progression of deficits and usually leads to death or severe disability over weeks or months. Instruct the patient of the importance of contacting their healthcare provider if they develop any symptoms suggestive of PML. Inform the patient that typical symptoms associated with PML are diverse, progress over days to weeks, and include progressive weakness on one side of the body or clumsiness of limbs, disturbance of vision, and changes in thinking, memory, and orientation leading to confusion and personality changes [see Warnings and Precautions (5.3)].

Malignancies

Advise patients that an increased risk of malignancy, including breast cancer, may exist with OCREVUS. Advise patients that they should follow standard breast cancer screening guidelines [see Warnings and Precautions (5.5)].

Immune-Mediated Colitis

Advise patients to promptly contact their healthcare provider if they experience any signs and symptoms of colitis, including diarrhea, abdominal pain, and blood in stool [see Warnings and Precautions (5.6)].

Liver Injury

Inform patients that liver injury has been reported with anti-CD20 B-cell depleting therapies, including OCREVUS. Instruct patients treated with OCREVUS to promptly report any symptoms that may indicate liver injury, including fatigue, anorexia, nausea, vomiting, right upper abdominal discomfort, dark urine, or jaundice. A blood test should be obtained before patients start therapy, and during treatment as clinically indicated [see Warnings and Precautions (5.7)].

Contraception

Females of childbearing potential should use effective contraception while receiving OCREVUS and for 6 months after the last infusion of OCREVUS [see Clinical Pharmacology (12.3)]. Instruct patients that if they are pregnant or plan to become pregnant while taking OCREVUS, they should inform their healthcare provider [see Use in Specific Populations (8.1)].

OCREVUS® [ocrelizumab]

Manufactured by:
Genentech, Inc.
A Member of the Roche Group
1 DNA Way
South San Francisco, CA 94080-4990

OCREVUS is a registered trademark of Genentech, Inc.
©2025 Genentech, Inc.

U.S. License No. 1048

MEDICATION GUIDE

OCREVUS® (oak-rev-us)
(ocrelizumab)
injection,
for intravenous use

What is the most important information I should know about OCREVUS?

OCREVUS can cause serious side effects, including:

- Infusion reactions: Infusion reactions are a common side effect of OCREVUS, which can be serious and may require you to be hospitalized. You will be monitored during your infusion and for at least 1 hour after each infusion of OCREVUS for signs and symptoms of an infusion reaction. Tell your healthcare provider or nurse if you get any of these symptoms:

- itchy skin
- rash
- hives
- tiredness
- coughing or wheezing

- trouble breathing
- throat irritation or pain
- feeling faint
- fever
- redness on your face (flushing)

- nausea
- headache
- swelling of the throat
- dizziness

- shortness of breath
- fatigue
- fast heart beat

These infusion reactions can happen for up to 24 hours after your infusion. It is important that you call your healthcare provider right away if you get any of the signs or symptoms listed above after each infusion.
If you get infusion reactions, your healthcare provider may need to stop or slow down the rate of your infusion.

- Infection:
  - Infections are a common side effect. OCREVUS increases your risk of getting upper respiratory tract infections, lower respiratory tract infections, skin infections, and herpes infections. Serious infections can happen with OCREVUS, which can be life-threatening or cause death. Tell your healthcare provider if you have an infection or have any of the following signs of infection including fever, chills, a cough that does not go away, or painful urination. Signs of herpes infection include:

- cold sores
- shingles

- genital sores
- skin rash

- pain
- itching

Signs of a more serious herpes infection include:

- changes in vision
- eye redness or eye pain

- severe or persistent headache
- stiff neck

- confusion

Signs of infection can happen during treatment or after you have received your last dose of OCREVUS. Tell your healthcare provider right away if you have an infection. Your healthcare provider should delay your treatment with OCREVUS until your infection is gone.

- Hepatitis B virus (HBV) reactivation: Before starting treatment with OCREVUS, your healthcare provider will do blood tests to check for hepatitis B viral infection. If you have ever had hepatitis B virus infection, the hepatitis B virus may become active again during or after treatment with OCREVUS. Hepatitis B virus becoming active again (called reactivation) may cause serious liver problems including liver failure or death. Your healthcare provider will monitor you if you are at risk for hepatitis B virus reactivation during treatment and after you stop receiving OCREVUS.
- Weakened immune system: OCREVUS taken before or after other medicines that weaken the immune system could increase your risk of getting infections.

- Progressive Multifocal Leukoencephalopathy (PML): PML is a rare brain infection that usually leads to death or severe disability, and has been reported with OCREVUS. Symptoms of PML get worse over days to weeks. It is important that you call your healthcare provider right away if you have any new or worsening neurologic signs or symptoms that have lasted several days, including problems with:

- thinking
- eyesight
- strength

- balance
- weakness on 1 side of your body
- using your arms or legs

- Decreased immunoglobulins: OCREVUS may cause a decrease in some types of antibodies. Your healthcare provider will do blood tests to check your blood immunoglobulin levels.

See "What are the possible side effects of OCREVUS?" for more information about side effects.

What is OCREVUS?

OCREVUS is a prescription medicine used to treat:

- relapsing forms of multiple sclerosis (MS), to include clinically isolated syndrome, relapsing-remitting disease, and active secondary progressive disease, in adults.
- primary progressive MS, in adults.

It is not known if OCREVUS is safe and effective in children.

Who should not receive OCREVUS?

- Do not receive OCREVUS if you have an active hepatitis B virus (HBV) infection.
- Do not receive OCREVUS if you have had a life-threatening allergic reaction to OCREVUS. Tell your healthcare provider if you have had an allergic reaction to OCREVUS or any of its ingredients in the past. See "What are the ingredients in OCREVUS?" for a complete list of ingredients in OCREVUS.

Before receiving OCREVUS, tell your healthcare provider about all of your medical conditions, including if you:

- have or think you have an infection. See "What is the most important information I should know about OCREVUS?"
- have ever taken, take, or plan to take medicines that affect your immune system, or other treatments for MS. These medicines could increase your risk of getting an infection.
- have ever had hepatitis B or are a carrier of the hepatitis B virus.
- have a history of inflammatory bowel disease or colitis.
- have a history of liver problems.
- have had a recent vaccination or are scheduled to receive any vaccinations.
  - You should receive any required 'live' or 'live-attenuated' vaccines at least 4 weeks before you start treatment with OCREVUS. You should not receive 'live' or 'live-attenuated' vaccines while you are being treated with OCREVUS and until your healthcare provider tells you that your immune system is no longer weakened.
  - When possible, you should receive any 'non-live' vaccines at least 2 weeks before you start treatment with OCREVUS. If you would like to receive any non-live (inactivated) vaccines, including the seasonal flu vaccine, while you are being treated with OCREVUS, talk to your healthcare provider.
  - If you have a baby and you received OCREVUS during your pregnancy, it is important to tell your baby's healthcare provider about receiving OCREVUS so they can decide when your baby should be vaccinated.
- are pregnant, think that you might be pregnant, or plan to become pregnant. It is not known if OCREVUS will harm your unborn baby. You should use birth control (contraception) during treatment with OCREVUS and for 6 months after your last infusion of OCREVUS. Talk with your healthcare provider about what birth control method is right for you during this time. Tell your healthcare provider if you become pregnant while receiving OCREVUS.
- are breastfeeding or plan to breastfeed. It is not known if OCREVUS passes into your breast milk. Talk to your healthcare provider about the best way to feed your baby if you take OCREVUS.

Tell your healthcare provider about all the medicines you take, including prescription and over-the-counter medicines, vitamins, and herbal supplements.

How will I receive OCREVUS?

- OCREVUS is given through a needle placed in your vein (intravenous infusion) in your arm.
- Before treatment with OCREVUS, your healthcare provider will give you a corticosteroid medicine and an antihistamine to help reduce infusion reactions (make them less frequent and less severe). You may also receive other medicines to help reduce infusion reactions. See "What is the most important information I should know about OCREVUS?"
- Your first full dose of OCREVUS will be given as 2 separate infusions, 2 weeks apart. Each infusion will last about 2 hours and 30 minutes.
- Your next doses of OCREVUS will be given as 1 infusion every 6 months. These infusions will last about 2 hours to 3 hours and 30 minutes depending on the infusion rate prescribed by your healthcare provider.

What are the possible side effects of OCREVUS?

OCREVUS may cause serious side effects, including:

- see "What is the most important information I should know about OCREVUS?"
- risk of cancers (malignancies) including breast cancer. Follow your healthcare provider's instructions about standard screening guidelines for breast cancer.
- Inflammation of the colon, or colitis: Tell your healthcare provider if you have any symptoms of colitis, such as:
  - Diarrhea (loose stools) or more frequent bowel movements than usual
  - Stools that are black, tarry, sticky or have blood or mucus
  - Severe stomach-area (abdomen) pain or tenderness
- Liver damage. OCREVUS may cause liver damage. Your healthcare provider will do blood tests to check your liver before you start OCREVUS and while you take OCREVUS if needed. Tell your healthcare provider right away if you have any symptoms of liver damage, such as:
  - yellowing of the skin and eyes (jaundice)
  - nausea
  - vomiting
  - unusual darkening of the urine
  - feeling tired or weak

These are not all the possible side effects of OCREVUS.
Call your doctor for medical advice about side effects. You may report side effects to FDA at 1-800-FDA-1088.

General information about the safe and effective use of OCREVUS.

Medicines are sometimes prescribed for purposes other than those listed in a Medication Guide. You can ask your pharmacist or healthcare provider for information about OCREVUS that is written for health professionals.

What are the ingredients in OCREVUS?

Active ingredient: ocrelizumab.

Inactive ingredients: glacial acetic acid, polysorbate 20, sodium acetate trihydrate, trehalose dihydrate.

Manufactured by: Genentech, Inc., A Member of the Roche Group, 1 DNA Way, South San Francisco, CA 94080-4990

U.S. License No. 1048

For more information, go to www.OCREVUS.com or call 1-844-627-3887.

This Medication Guide has been approved by the U.S. Food and Drug Administration

Revised: 8/2025

Representative sample of labeling (see the HOW SUPPLIED section for complete listing):

PRINCIPAL DISPLAY PANEL - 300 mg/10 mL Vial Carton

NDC 50242-150-01

Ocrevus®
(ocrelizumab)
Injection

300 mg/10 mL
(30 mg/mL)

For Intravenous Infusion.
Must Be Diluted.

Single-Dose Vial.
Discard Unused Portion.

Attention Pharmacist: Dispense the
accompanying Medication Guide to each
patient.

Rx only

1 vial

Genentech

10233065